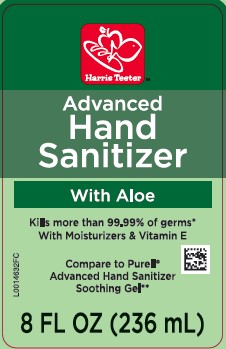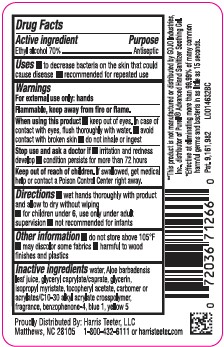 DRUG LABEL: Advanced Hand Sanitizer
NDC: 72036-439 | Form: GEL
Manufacturer: Harris Teeter
Category: otc | Type: HUMAN OTC DRUG LABEL
Date: 20260204

ACTIVE INGREDIENTS: ALCOHOL 70 mL/100 mL
INACTIVE INGREDIENTS: WATER; ALOE VERA LEAF; GLYCERYL CAPRYLATE/CAPRATE; GLYCERIN; ISOPROPYL MYRISTATE; .ALPHA.-TOCOPHEROL ACETATE; CARBOMER INTERPOLYMER TYPE A (ALLYL SUCROSE CROSSLINKED); SULISOBENZONE; FD&C BLUE NO. 1; FD&C YELLOW NO. 5

Harris Teeter 439.001/439AB-AC rev 1
Advanced Hand Sanitizer with Aloe

Active ingredient

Ethyl Alcohol 70%

Purpose

Antiseptic

Uses

- to decrease bacteria on the skin that could cause disease
- recommended for repeated use

Warnings

For external use only: hands

Flammable, keep away from heat and flame.

When using this product

- keep out of eyes. In case of contact with eyes, flush thoroughly with water.
- avoid contact with broken skin
- do not inhale or ingest

Stop use and ask a doctor if

- irritation and redness develop
- conditiion persists for more than 72 hours

Keep out of reach of children.

If swallowed, get medical help or contact a Poison Control Center right away.

Directions

- wet hands thoroughly with product and allow to dry without wiping
- for children under 6, use only under adult supervision
- not recommended for infants

Other information

- do not store above 105⁰ F
- may discolor some fabrics
- harmful to wood finishes and plastics

Inactive ingredients

water, aloe, barbadensis leaf juice, glyceryl caprylate/caprate, glycerin, isopropyl myristate, tocopheryl acetate, acrylates/C10-30 alkyl acrylate crosspolymer, fragrance, benzophenone-4, blue 1, yellow 5

Disclaimer/Claim

**This product is not manufactured or distributed by GOJO Industries, Inc. distributor of PurellAdvanced Hand Sanitizer Soothing Gel.

*Effective at eliminating more than 99.99% of many common harmful germs and bacteria in as little as 15 seconds.

ADVERSE REACTION

Proudly Distributed By: Harris Teeter, LLC

Matthews, NC 28105

1-800-432-6111 or harristeeter.com

Pat. 9,161,982

principal display panel

Harris Teeter™

Advanced Hand Sanitizer

With Aloe

Kills more than 99.99% of germs*

With Moisturizers & Vitamin E

Compare to Purell® Advanced Hand Sanitizer Soothing Gel**

8 FL OZ (236 mL)